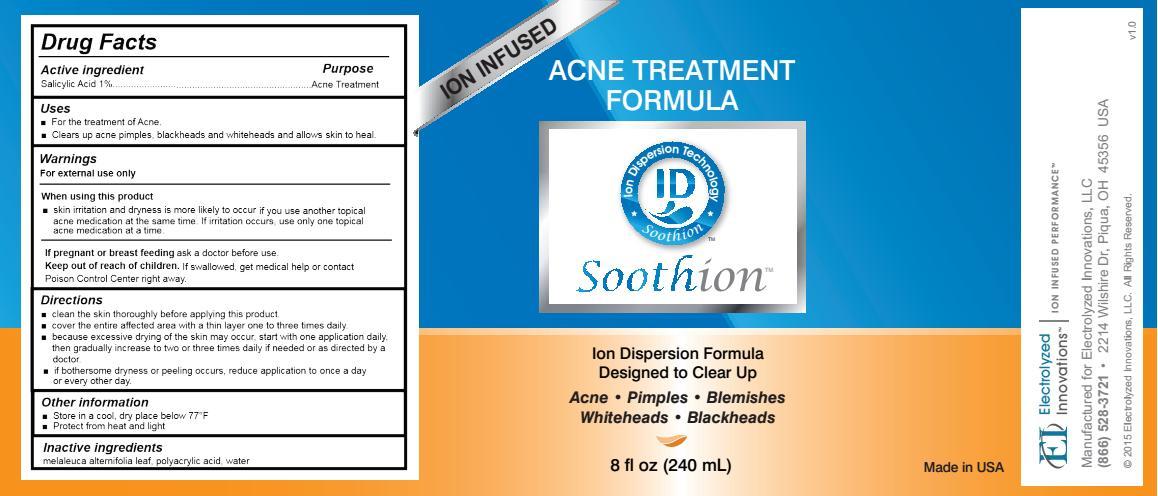 DRUG LABEL: Soothion Acne Treatment Formula
NDC: 69031-005 | Form: LOTION
Manufacturer: Electrolyzed Innovations, LLC
Category: otc | Type: HUMAN OTC DRUG LABEL
Date: 20191223

ACTIVE INGREDIENTS: SALICYLIC ACID 1 g/100 g
INACTIVE INGREDIENTS: MELALEUCA ALTERNIFOLIA LEAF; POLYACRYLIC ACID (250000 MW); WATER

Drug Facts

Active ingredient

Salicylic acid 1%

Purpose

Acne Treatment

Uses

- For the treatment of Acne.
- Clears up acne pimples, blackheads and whiteheads and allows skin to heal.

Warnings

For external use only.

When using this product

- skin irritation and dryness is more likely to occur if you use another topical acne medication at the same time. If irritation occurs, only use one topical acne medication at a time.

PREGNANCY OR BREAST FEEDING

If pregnant or breast feeding ask a doctor before use.

Keep out of reach of children. If swallowed, get medical help or contact Poison Control Center right away.

Directions

- clean the skin thoroughly before applying this product.
- cover the entire affected area with a thin layer one to three times a daily.
- because excessive drying of the skin may occur, start with one application daily, then gradually increase to two or three times daily if needed or as directed by a doctor.
- if bothersome dryness or peeling occurs, reduce application to once a day or every other day.

Other information

- Store in a cool, dry place below 77°F
- Protect from heat and light

Inactive ingredients

melaleuca alternifolia leaf, polyacrylic acid, water

DESCRIPTION

Manufactured for Electrolyzed Innovations, LLC
(866) 528-3721 2214 Wilshire Dr, Piqua OH 45356 USA

Principal Display Panel

Ion Infused
Acne Treatment Formula

Soothion

Ion Disperson Formula Designed to Clear Up

- Acne
- Pimples
- Blemishes
- Whiteheads
- Blackheads

Net Wt. 8 oz (240 mL) Made in USA